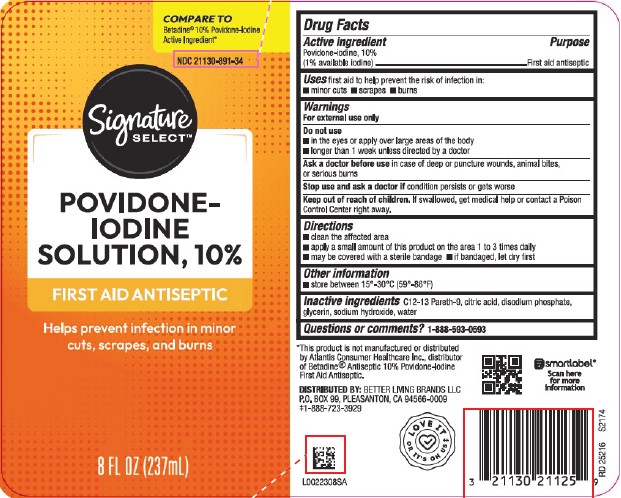 DRUG LABEL: First Aid Antiseptic
NDC: 21130-891 | Form: SOLUTION
Manufacturer: Better Living Brands, LLC
Category: otc | Type: HUMAN OTC DRUG LABEL
Date: 20260223

ACTIVE INGREDIENTS: POVIDONE-IODINE 10 mg/1 mL
INACTIVE INGREDIENTS: C12-13 PARETH-9; CITRIC ACID MONOHYDRATE; SODIUM PHOSPHATE, DIBASIC, ANHYDROUS; GLYCERIN; SODIUM HYDROXIDE; WATER

Signature Select 050.002/050AE
Povidone-Iodine Solution, 10%

Active ingredient

Povidone-iodine, 10% (1% available iodine)

Purpose

First aid antiseptic

Uses

first aid to help prevent the risk of infection in:

- minor cuts
- scrapes
- burns

Warnings

For external use only

Do not use

- in the eyes or apply over large areas of the body
- longer than 1 week unless directed by a doctor

Ask a doctor before use

in case of deep or puncture wounds, animal bites, or serious burns

Stop use and ask a doctor if

condition persists or gets worse

Keep out of reach of children.

If swallowed, get medical help or contact a Poison Control Center right away.

Directions

- clean the affected area
- apply a small amount of this product on the area 1 to 3 times daily
- may be covered with a sterile bandage
- if bandaged, let dry first

Other information

- store between 15º-30ºC (59º-86ºF)

Inactive ingredients

C12-13 Pareth-9, citric acid, disodium phosphate, glycerin, sodium hydroxide, water

Questions or comments?

1-888-593-0593

Disclaimer

*This product is not manufactured or distributed by Atlantis Consumer Healthcare Inc., distributor of Betadine®Antiseptic 10% Povidone-Iodine First Aid Antiseptic.

Adverse Reaction

DISTRIBUTED BY: BETTER LIVING BRANDS LLC

P.O. BOX 99, PLEASANTON, CA 94566-0009

‡1-888-723-3929

LOVE IT OR IT'S ON US‡

smartlabel

Scan here for more information

Principal Display Panel

Compare to Betadine®10% Povidone-Iodine Active Ingredient*

NDC 21130-891-34

Signature SELECT™

POVIDONE-IODINE SOLUTION, 10%

FIRST AID ANTISEPTIC

Helps prevent infection in minor cuts, scrapes, and burns

8 FL OZ (237 mL)